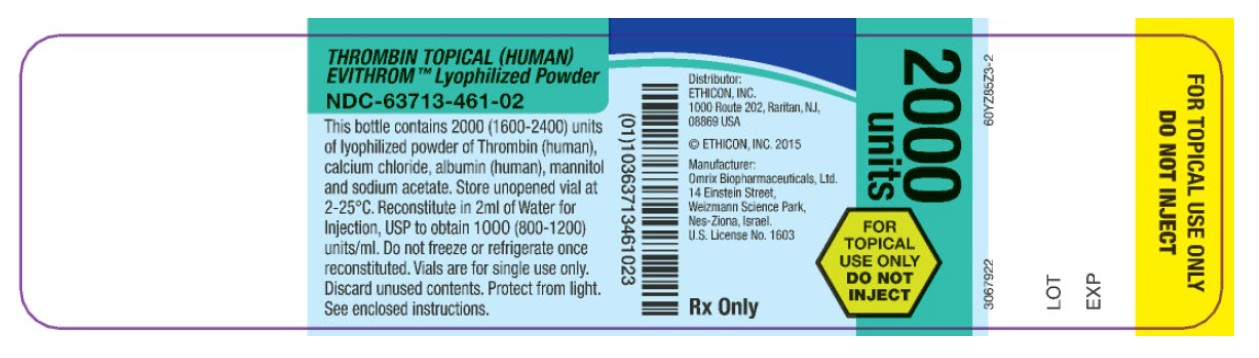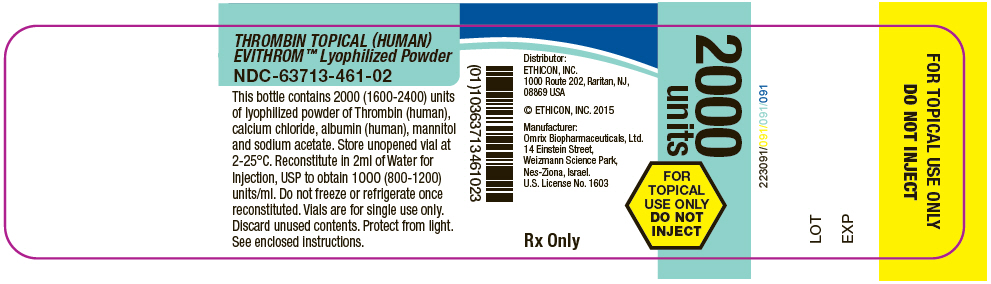 DRUG LABEL: thrombin human
NDC: 63713-461 | Form: POWDER, FOR SOLUTION
Manufacturer: Ethicon, Inc
Category: other | Type: PLASMA DERIVATIVE
Date: 20250611

ACTIVE INGREDIENTS: HUMAN THROMBIN 2000 [iU]/2 mL
INACTIVE INGREDIENTS: ALBUMIN HUMAN; CALCIUM CHLORIDE; MANNITOL; SODIUM ACETATE

HIGHLIGHTS OF PRESCRIBING INFORMATION

These highlights do not include all the information needed to use EVITHROM™ safely and effectively. See full prescribing information for EVITHROM™.
EVITHROM™ [Thrombin, Topical (Human)]
Lyophilized Powder for Solution
For topical use
Initial U.S. Approval: 2007

1 INDICATIONS AND USAGE

- EVITHROM™ is a topical thrombin indicated as an aid to hemostasis whenever oozing blood and minor bleeding from capillaries and small venules is accessible and control of bleeding by standard surgical techniques (such as suture, ligature or cautery) is ineffective or impractical (1).
- EVITHROM™ may be used in conjunction with an Absorbable Gelatin Sponge, USP (1).

2 DOSAGE AND ADMINISTRATION

- For topical use only. DO NOT INJECT(2.2).
- Apply EVITHROM™ on the surface of bleeding tissue only.
- The amount of EVITHROM™ required depends upon the area of tissue to be treated and the method of application. In clinical studies, volumes up to 10 ml were used in conjunction with Absorbable Gelatin Sponge, USP (2.2).

3 DOSAGE FORMS AND STRENGTHS

EVITHROM™ is a lyophilized powder for solution containing 2000 (1600-2400) units of human thrombin. After reconstituted the final solution contains 1000 (800-1200) units/ml of EVITHROM™ (3).

4 CONTRAINDICATIONS

- Do not use in individuals known to have an anaphylactic or severe systemic reaction to EVITHROM™ or to human blood products(4) .
- Do not use for treatment of severe or brisk arterial bleeding(4) .

5 WARNINGS AND PRECAUTIONS

- Potential risk of thrombosis if absorbed systemically(5.1) .
- May carry a risk of transmitting infectious agents such as viruses and theoretically, the Creutzfeldt-Jakob disease (CJD) agent, despite manufacturing steps designed to reduce the risk of viral transmission(5.2) .
- Hypersensitivity reactions, including anaphylaxis, may occur(5.1) .

6 ADVERSE REACTIONS

- The most common adverse reactions (incidence 2%) were prolonged activated partial thromboplastin time, increased INR, decreased lymphocyte count, prolonged prothrombin time and increased neutrophil count (6).
- None of the patients treated with EVITHROM™ developed antibodies to human thrombin or to human Factor V/Va. The clinical significance of these findings is unknown (6).

To report SUSPECTED ADVERSE REACTIONS, contactETHICON Customer Support Center at (877) 384-4266 or FDA at 1-800-FDA-1088 or www.fda.gov/medwatch.

8 USE IN SPECIFIC POPULATIONS

Animal Reproduction studies have not been conducted with EVITHROM™. EVITHROM™ should only be used in pregnancy if clearly indicated (8.1).

FULL PRESCRIBING INFORMATION

1 INDICATIONS AND USAGE

EVITHROM™ Thrombin, Topical (Human), is indicated as an aid to hemostasis whenever oozing blood and minor bleeding from capillaries and small venules is accessible and control of bleeding by standard surgical techniques (such as suture, ligature or cautery) is ineffective or impractical.

EVITHROM™ Thrombin, Topical (Human), may be used in conjunction with an Absorbable Gelatin Sponge, USP.

2 DOSAGE AND ADMINISTRATION

2.1 Dose

For Topical Use Only. DO NOT INJECT.

The amount of EVITHROM™ required depends upon the area of tissue to be treated and the method of application. As an approximate guide, volumes up to 10 ml were used in clinical studies where EVITHROM™ was used in conjunction with Absorbable Gelatin Sponge, USP.

2.2 Preparation

- Use aseptic technique when handling vials and syringes.
- Remove the flip-off plastic cap from the vial to expose the rubber stopper.
- Reconstitute the lyophilized human thrombin powder with 2 ml of sterile Water for Injection, USP using the provided reconstitution device.
- Shake gently until the solution is clear.
- Reconstituted solution is stable for up to 8 hours at room temperature and should be used within this time period.

2.3 Application Techniques

Apply only on the surface of bleeding tissue.

EVITHROM™ Use alone

- Sponge target surface (do not wipe) or suction free of blood before application.
- Flood the surface with EVITHROM™ using a sterile syringe and small gauge needle.
- Avoid sponging after treatment, to ensure that the clot remains securely in place.

EVITHROM™ in conjunction with Absorbable Gelatin Sponge, USP

- Prepare the desired shape of the Absorbable Gelatin Sponge, USP. (see Absorbable Gelatin Sponge, USP circular for additional instructions for use).
- Transfer EVITHROM™ into a sterile container using aseptic techniques.
- Immerse gelatin sponge into the EVITHROM™ solution.
- Vigorously knead the sponge with moistened gloved fingers until all air is expelled and it can return to its original size and shape.
- Hold the saturated sponge in place with gauze or cotton pledget using moderate pressure until hemostasis is achieved.

3 DOSAGE FORMS AND STRENGTHS

EVITHROM™ is a sterile lyophilized powder for solution 2000 (1600-2400) units of lyophilized human thrombin powder for reconstitution. After reconstituted, the final solution contains 1000 (800-1200) units/ml of human thrombin.

Potency, expressed in units, is determined using a clotting assay against an internal reference standard for potency that has been calibrated against the World Health Organisation (WHO) Second International Standard for Thrombin, 01/580. Therefore, a unit used herein is equivalent to an International Unit.

4 CONTRAINDICATIONS

- Do not use in individuals known to have an anaphylactic or severe systemic reaction to EVITHROM™ or to human blood products.
- Do not use for the treatment of severe or brisk arterial bleeding.

5 WARNINGS AND PRECAUTIONS

5.1 Thrombosis

There is a risk of thrombosis if absorbed systemically. Apply topically only.

5.2 Anaphylactic/Hypersensitivity Reactions

Anaphylactic reactions may occur in rare cases. No adverse events of this type were reported during the conduct of the clinical trials. Severe hypotensive reactions require immediate intervention using current principles of shock therapy.

5.3 Transmission of Infectious Agents

Because this product is made from human plasma, it may carry a risk of transmitting infectious agents, such as viruses, and theoretically, the Creutzfeldt-Jakob disease (CJD) agent. The risk of transmitting an infectious agent has been reduced by screening plasma donors for prior exposure to certain viruses, by testing for the presence of certain current virus infections and by inactivating and removing certain viruses. Despite these measures, such products can still potentially transmit disease. There is also the possibility that unknown infectious agents may be present in such products.

6 ADVERSE REACTIONS

The most common adverse reactions during clinical trial (reported in at least 2% of subjects treated with EVITHROM™) were prolonged activated partial thromboplastin time, increased INR, decreased lymphocyte count, prolonged prothrombin time and increased neutrophil count.

6.1 Clinical Trials Experience

Because clinical trials are conducted under widely varying conditions, adverse reaction rates observed in the clinical trials of a drug product cannot be directly compared to rates in the clinical trials of another drug and may not reflect the rates observed in clinical practice.

In a multicenter, prospective, controlled, randomized, double-blinded clinical trial of 305 subjects where EVITHROM™ (n=153) was compared with bovine thrombin (n=152), occurrence of adverse events was not statistically different between the two groups.

Overall, adverse events occurred in similar proportions of subjects in the two groups (see Table 1). No clinically significant differences were seen in age (<65 years, >65 years) or gender subgroup analyses of adverse events.

At least one serious adverse event (SAE) was reported for 26/153 (17%) subjects treated with human thrombin and 17/152 (11%) subjects treated with bovine thrombin. The SAEs reported were associated with post-surgical complications (e.g. wound infection 3/153 for EVITHROM™ and 2/152 for bovine thrombin) and the medical condition of the subject and were not considered related to study drug. Two subjects (1.3%) in EVITHROM™ group experienced a treatment emergent severe adverse event: respiratory arrest and post-procedural hematoma (in one subject) and extradural hematoma. Three subjects in the bovine thrombin group experienced a treatment emergent severe adverse event: hyperhidrosis, pyrexia and post-procedural hematoma.

No deaths were reported during the study period.

Viral serology was not monitored during the trial with EVITHROM™. However, no adverse events indicative of infection with transfusion-transmissible agents were reported.

Table 1: Incidence of subjects with related adverse events reported in at least 2% of subjects treated with either human or bovine thrombin
 | Thrombin Type
System Organ Class/Adverse Event | EVITHROM™ (n=153) | Bovine (n=152) | Total (n=305)
Investigations | 11 (7.2%) | 14 (9.2%) | 25 (8.2%)
Activated partial thromboplastin time increased | 4 (2.6%) | 8 (5.3%) | 12 (3.9%)
International normalized ratio increased | 4 (2.6%) | 5 (3.3%) | 9 (3.0%)
Lymphocyte count decreased | 4 (2.6%) | 2 (1.3%) | 6 (2.0%)
Prothrombin time prolonged | 4 (2.6%) | 8 (5.3%) | 12 (3.9%)
Neutrophil count increased | 3 (2.0%) | 2 (1.3%) | 5 (1.6%)
Skin and Subcutaneous Tissue Disorders | 1 (0.7%) | 3 (2.0%) | 4 (1.3%)
Pruritus | 1 (0.7%) | 3 (2.0%) | 4 (1.3%)
General Disorders and Administration Site Conditions | 0 | 3 (2.0%) | 3 (1.0%)

Immunogenicity

In the clinical study, serum samples were collected at baseline and at 5 weeks post-surgery for evaluation of antibodies to bovine thrombin, bovine Factor V/Va, human thrombin, and human Factor V/Va. Samples were collected at both time points for 81.3% of the subjects. The ELISA data were adjudicated by a panel of experts blinded to treatment assignment. After reviewing all data, the panel used an algorithm for assigning outcomes for each antigen: seroconversion negative or seroconversion positive.

The protocol did not specify any comparative analysis for immunogenicity data, only descriptive statistics. The adjudicated results show that 3.3% of the subjects treated with EVITHROM™ (frozen formulation) developed antibodies to any of the four antigens, compared to 12.7% of the subjects developing antibodies in the control group (bovine thrombin). 7.9% of the subjects treated with bovine thrombin (control group) developed antibodies to bovine thrombin and 9.5% of these subjects developed antibodies to bovine Factor V/Va. A few control subjects had antibodies that cross-reacted with human thrombin, but none had antibodies that crossreacted with human Factor V/Va. None of the patients treated with EVITHROM™ developed detectable antibodies to human thrombin or to human Factor V/Va.

The detection of antibody formation is highly dependent upon the sensitivity and specificity of the assay. The observed incidence of a positive signal in an assay may be influenced by several factors including timing of sampling, sample handling, concomitant medications, or underlying disease. Therefore, direct comparison of incidence of antibody development to human thrombin, bovine thrombin, human Factor V/Va or bovine Factor V/Va following administration of EVITHROM™ with incidence of antibody development following administration of other products may be misleading and the clinical significance of these findings is unknown.

6.2 Post Marketing Experience

No adverse reactions have been identified from spontaneous post-marketing reports.

8 USE IN SPECIFIC POPULATIONS

8.1 Pregnancy

Risk Summary

There are no data with EVITHROM™ use in pregnant women to inform a drug-associated risk.

Animal reproduction studies have not been conducted with EVITHROM™. It is not known whether EVITHROM™ can cause fetal harm when administered to a pregnant woman or can affect reproduction capacity. EVITHROM™ should be given to a pregnant woman only if clearly needed. In the U.S. general population, the estimated background risk of major birth defect and miscarriage in clinically recognized pregnancies is 2-4% and 15-20%, respectively.

8.2 Lactation

Risk Summary

There is no information regarding the presence of EVITHROM™ in human milk, the effect on the breastfed infant, or the effects on milk production. The developmental and health benefits of breastfeeding should be considered along with the mother's clinical need for EVITHROM™ and any potential adverse effects on the breastfed infant from EVITHROM™ or from the underlying maternal condition.

8.4 Pediatric Use

Of the 155 patients undergoing liver surgery who were treated in adequate and well-controlled studies of EVICEL™ Fibrin Sealant (Human), in which EVITHROM™ is a component, eight were pediatric patients. Of these, five were less than 2 years old and three were between 2 and 12 years old. Use of EVITHROM™ in pediatric patients is supported by these data and by extrapolation of findings for safety and efficacy in adults.

8.5 Geriatric Use

Sixty three (63) subjects over 65 years of age received EVITHROM™ in the clinical trial.

No differences in safety or effectiveness were observed between the elderly and younger patients. Greater susceptibility of older patients to adverse reactions cannot be ruled out.

11 DESCRIPTION

EVITHROM™ is a sterile lyophilized powder of purified human thrombin (1600-2400 units) of white to slightly yellowish color. When reconstituted, EVITHROM™ solution, pH 6.8-7.2, is clear to slightly opalescent and colorless to slightly yellowish. Other inactive ingredients are Calcium chloride, Human albumin, Mannitol, Sodium acetate

EVITHROM™ is made from pooled Human Source obtained from US licensed plasma collection centers. Individual plasma units obtained for production of EVITHROM™ are tested by licensed serological tests for HBsAg, HIV 1 & 2 Ab and HCV Ab. Additionally, the plasma units are tested by licensed Nucleic Acid Testing (NAT) for HIV-1, HCV, HBV, HAV and parvovirus B19. All tests for HIV, HCV, HBV and HAV must be negative (non-reactive). However, since the effectiveness of the HBV and HAV NAT methods in detecting low levels of viral material is still under investigation, the significance of a negative result for these viruses is unknown. The level of parvovirus B19 contamination is not permitted to exceed 10,000 copies/ml. This limit is applied to restrict the viral load of parvovirus B19 in the starting plasma pool. In addition to the screening of plasma units, each manufacturing pool is tested for HBsAg, HIV-1 & 2 Ab, HCV NAT and for parvovirus B19 by NAT. Manufacturing pool testing, however, is of lower sensitivity than individual unit testing.

EVITHROM™ is manufactured by purification of prothrombin from cryo-poor plasma followed by activation with calcium chloride, or alternatively with calcium chloride in combination with Gluconate. The manufacturing process includes two targeted steps for inactivation or removal of viruses. The first of these is treatment with a solvent/detergent (S/D) mixture (1% tri-n-butyl phosphate and 1% Triton X-100 or 1% Polysorbate-80 and 0.3% tri-n-butyl phosphate) for 6 hours at 26°C to inactivate lipid enveloped viruses. The S/D reagents are removed by cation exchange chromatography. Mannitol and human albumin are used to stabilize the solution, which undergoes nanofiltration for removal of both enveloped and non-enveloped viruses. After nanofiltration, the solution is formulated with calcium chloride, sterile filtered and aseptically filled and frozen.

The effectiveness of the S/D treatment and nanofiltration procedures for reducing virus content has been assessed using a series of viruses with a range of physico-chemical characteristics. The results of the validation studies are summarized in Table 2.

Table 2: Reducing factors of S/D treatment and nanofiltration for a series of viruses
Virus | HIV-1 | BVDV | PRV | EMCV | HAV | MVM | PPV
 | Reduction factor (log10)
SD Treatment | ≥5.5 | >4.6 | >4.2 | Not Done | Not Done | Not Done | Not Done
Nanofiltration | ≥4.6 | ≥5.6 | ≥5.7 | ≥7.4 | ≥7.5 | ≥6.3 | ≥ 5.6
Global Reduction Factor | ≥10.1 | ≥10.2 | ≥9.9 | ≥7.4 | ≥7.5 | ≥6.3 | ≥5.6
HIV-1: Human Immunodeficiency Virus Type 1;
BVDV: Bovine Viral Diarrhea Virus;
PRV: Pseudorabies Virus;
EMCV: Encephalomyocarditis Virus;
HAV: Hepatitis A Virus;
MVM: Minute Virus of Mouse;
PPV: Porcine Parvovirus

12 CLINICAL PHARMACOLOGY

EVITHROM™ requires no intermediate physiological agent because it clots the fibrinogen of the blood directly. Failure to clot blood occurs in the rare case where the primary clotting defect is the absence of fibrinogen itself. The speed with which thrombin clots blood is dependent upon the concentration of both thrombin and fibrinogen.

12.1 Mechanism of Action

Thrombin (coagulation Factor IIa) is a highly specific protease that transforms plasma fibrinogen into fibrin which, in the presence of Factor XIII in the patient's plasma, is cross-linked to form a stable clot. When applied to a surgical wound where bleeding is present, thrombin activates fibrinogen in the patient's plasma to form fibrin, which results in clot formation and hemostasis. The fibrin clot is stabilized by cross-linking occurring as a result of activation of the patient's endogenous Factor XIII, which requires the presence of calcium.

13 NONCLINICAL TOXICOLOGY

13.1 Carcinogenesis, Mutagenesis, Impairment of Fertility

Long-term animal studies have not been performed to evaluate the carcinogenic potential of EVITHROM™ due to the human origin of thrombin.

Studies were performed in bacteria to determine mutagenicity of human thrombin alone, and solvent/detergent residues [tri-n-butyl phosphate (TnBP) and Triton X-100], used in the virus inactivation manufacturing step. These studies were negative for both thrombin and for TnBP or Triton X-100 at all concentrations tested. All concentrations of the combination of TnBP and Triton X-100 also tested negative in assays performed to determine mammalian cell mutagenicity, chromosomal aberrations and micronuclei induction. No study was performed for Polysorbate-80 and tri-n-butyl phosphate.

The effect of EVITHROM™ on fertility has not been evaluated. Reproductive studies were performed in rats with the combination of solvent detergent impurities, TnBP and Triton X-100 at doses up to approximately 600-fold human dose of TnBP (900 µg/kg/day) and 3000-fold human dose of Triton X-100 (4500 µg/kg/day) resulted in increased post-implantation loss and an increased number of late resorptions. Other studies performed with combinations of TnBP (300-fold human dose, 450 µg/kg/day) and Triton X-100 (1500-fold human dose, 2250 µg/kg/day) resulted in increased resorption rates, decreased fetal body weights, and an increased number of runts. No embryo-fetal adverse effects were observed at doses up to 300 µg/kg/day TnBP and 1500 µg/kg/day Triton X-100, 200-fold and 1000-fold the human dose, respectively.

13.2 Animal Toxicology and/or Pharmacology

EVICEL Fibrin Sealant (Human), which includes EVITHROM™ as one of the active components, was classified as non-irritant in the Primary Cutaneous Irritation Test and slightly irritant in the Ocular Irritation test.

Neurotoxicity studies performed with EVITHROM™ or with EVICEL confirmed that intracerebral application of thrombin was not associated with any evidence of neurotoxicity.

No toxicological effects due to solvent/detergent reagents [tri-n-butyl phosphate (TnBP) and Triton X-100] used in the virus inactivation procedure are expected since the residual levels are less than 5 µg/ml. This evaluation was not performed for Polysorbate-80.

14 CLINICAL STUDIES

EVITHROM™ was compared with bovine thrombin in a multicenter, prospective, randomized, controlled, double-blinded clinical trial of 305 subjects at 22 centers in the US. Subjects undergoing elective cardiovascular, neurologic (spinal) or general surgical procedures were randomized (stratified by surgical specialty) when there was oozing or bleeding of mild intensity that could not be controlled by other surgical techniques and the surgeon determined that a topical hemostatic agent was necessary. Bovine thrombin and EVITHROM™ were applied with SURGIFOAM™ Absorbable Gelatin Sponge, USP.

Treatment with EVITHROM™ was comparable to treatment with bovine thrombin in achieving hemostasis within:

- 10 minutes of product application and
- 6 and 3 minutes of product application.

Table 3: Efficacy for Intent to Treat (ITT) population
Time Interval | Treatment Group: # Successes/N (%) |  | Ratio Human/Bovine | 95% CI for Ratio Human/Bovine [95% CI is for the ratio of proportions of success] , [For the two treatments to be equivalent, both limits of the confidence interval must have been within (0.80, 1.25)]
Time Interval | EVITHROM™ N=153 | Bovine thrombin N=152 | Ratio Human/Bovine | 95% CI for Ratio Human/Bovine [95% CI is for the ratio of proportions of success] , [For the two treatments to be equivalent, both limits of the confidence interval must have been within (0.80, 1.25)]
10 minutes | 149/153 (97.4) | 148/152 (97.4) | 1.00 | 0.96, 1.05
6 minutes | 145/153 (94.8) | 141/152 (92.8) | 1.02 | 0.96, 1.09
3 minutes | 112/153 (73.2) | 110/152 (72.4) | 1.01 | 0.88, 1.16

Table 4: Efficacy at 6 minutes (ITT population)
Surgical Specialty | Treatment Group: # Successes/N (%) |  | Ratio Human/Bovine | 95% CI for Ratio Human/Bovine [95% CI is for the ratio of proportions of success] , [For the two treatments to be equivalent, both limits of the confidence interval must have been within (0.80, 1.25)]
Surgical Specialty | EVITHROM™ | Bovine thrombin | Ratio Human/Bovine | 95% CI for Ratio Human/Bovine [95% CI is for the ratio of proportions of success] , [For the two treatments to be equivalent, both limits of the confidence interval must have been within (0.80, 1.25)]
Cardiovascular | 44/47 (93.6) | 38/46 (82.6) | 1.13 | 0.97, 1.36
Neurosurgical (Spine) | 60/61 (98.4) | 59/60 (98.3) | 1.00 | 0.93, 1.08
General Surgery | 41/45 (91.1) | 44/46 (95.7) | 0.95 | 0.82, 1.08
Overall | 145/153 (94.8) | 141/152 (92.8) | 1.02 | 0.96, 1.09

At the 6 minute and 10 minute time points, >90% of subjects from all surgeries in both study groups had achieved hemostasis. The following results were documented for the 3 minute time point as stratified by surgery and study treatment: (1) cardiovascular surgery - human thrombin: 61.7%; bovine thrombin: 63.0%, (2) spinal surgery - human thrombin: 83.6%; bovine thrombin: 80.0%, (3) general surgery - human thrombin: 71.1%; bovine thrombin: 71.7% for an overall ratio of proportions of 1.01.

16 HOW SUPPLIED/STORAGE AND HANDLING

EVITHROM™ is supplied in a single-use 2 ml vial containing 2000 (1600-2400) units of lyophilized human thrombin powder for reconstitution in 2 ml Water for Injection, USP.

NDC 63713-461-02

STORAGE AND HANDLING

- Store EVITHROM™ powder vials at 2- 25°C (36-77°F) for up to 2 years.
- Discard if the packaging of EVITHROM™ is damaged.
- Keep the vials protected from light.
- Store reconstituted EVITHROM™ solution at room temperature for up to 8 hours.
- Do not freeze or refrigerate EVITHROM™ once it has been reconstituted.
- Discard unused contents.

17 PATIENT COUNSELING INFORMATION

Inform patients of the following:

- Some viruses such as hepatitis A virus and parvovirus B19 are particularly difficult to remove or inactivate. Parvovirus B19 most seriously affects pregnant women or immune-compromised individuals. Symptoms of parvovirus B19 infection include: fever, drowsiness, chills and runny nose followed about two weeks later by a rash and joint pain. Evidence of hepatitis A may include several days to weeks of poor appetite, fatigue and low-grade fever followed by nausea, vomiting and abdominal pain. Dark urine and a yellowed complexion are also common symptoms. Consult your physician if such symptoms appear.
- If absorbed systemically EVITHROM™ could potentially cause blood clotting disorders. Consult your physician if leg tenderness or swelling, chest pain, or shortness of breath appears.

Distributed by:
Ethicon, Inc.
1000 Route 202, Raritan,
NJ, 08869 USA

Manufactured by:
Omrix Biopharmaceuticals Ltd.
14 Einstein Street, Weizmann Science
Park, Nes-Ziona, Israel

U.S. License No. 1603
Ethicon, Inc. 2019
© Omrix Biopharmaceuticals Ltd., 2019

Art. No. 83YZ00Z3D1

PRINCIPAL DISPLAY PANEL - 2 ml Vial Label - Grifols

THROMBIN TOPICAL (HUMAN)
EVITHROM ™ Lyophilized Powder

NDC-63713-461-02

This bottle contains 2000 (1600-2400) units
of lyophilized powder of Thrombin (human),
calcium chloride, albumin (human), mannitol
and sodium acetate. Store unopened vial at
2-25°C. Reconstitute in 2ml of Water for
Injection, USP to obtain 1000 (800-1200)
units/ml. Do not freeze or refrigerate once
reconstituted. Vials are for single use only.
Discard unused contents. Protect from light.
See enclosed instructions.

PRINCIPAL DISPLAY PANEL - 2 ml Vial Label - Patheon

THROMBIN TOPICAL (HUMAN)
EVITHROM ™ Lyophilized Powder

NDC-63713-461-02

This bottle contains 2000 (1600-2400) units
of lyophilized powder of Thrombin (human),
calcium chloride, albumin (human), mannitol
and sodium acetate. Store unopened vial at
2-25°C. Reconstitute in 2ml of Water for
Injection, USP to obtain 1000 (800-1200)
units/ml. Do not freeze or refrigerate once
reconstituted. Vials are for single use only.
Discard unused contents. Protect from light.
See enclosed instructions.